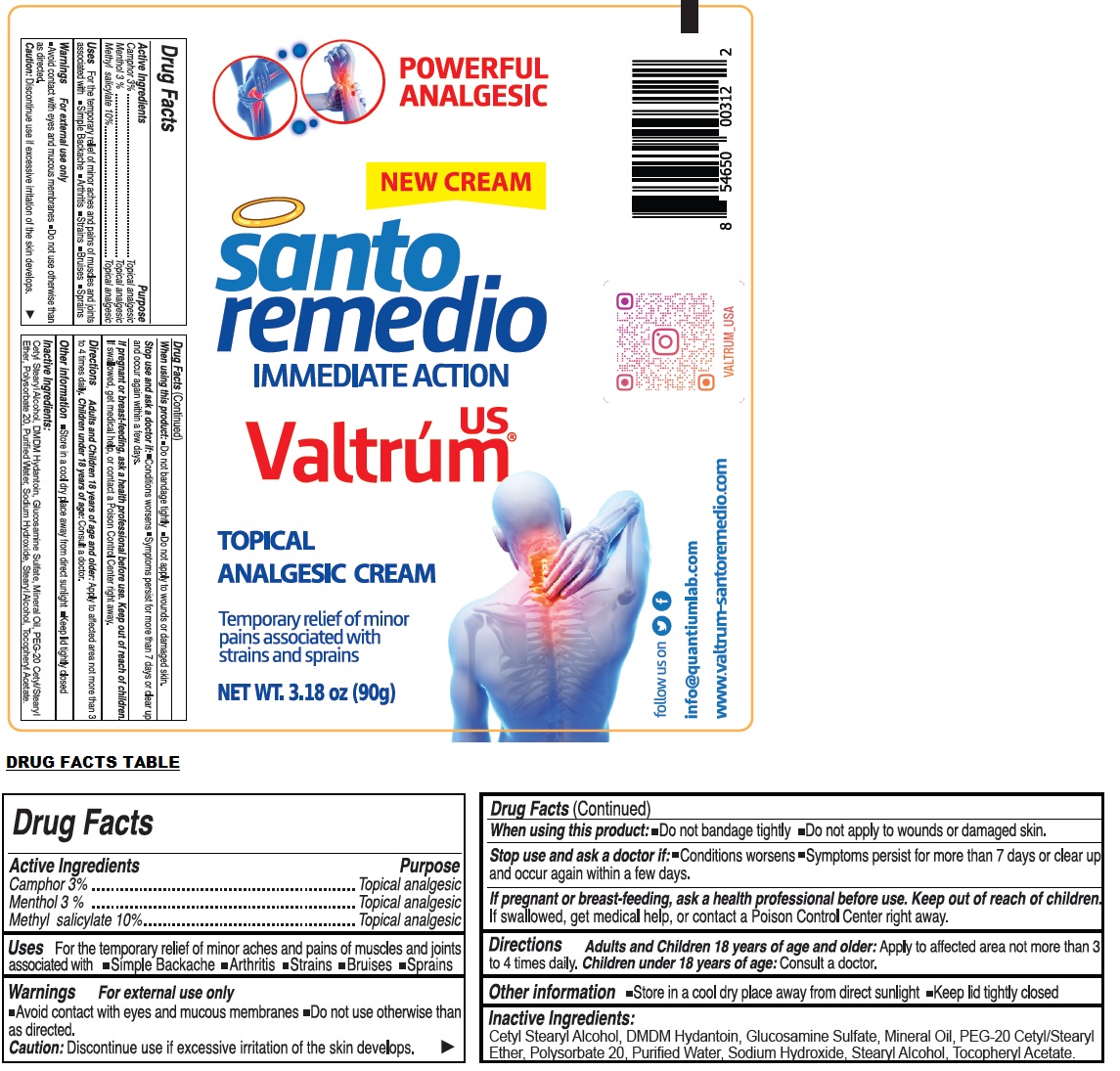 DRUG LABEL: Valtrum IMMEDIATE ACTION TOPICAL ANALGESIC
NDC: 75849-897 | Form: CREAM
Manufacturer: LABORATORIOS QUANTIUM LLC
Category: otc | Type: HUMAN OTC DRUG LABEL
Date: 20231221

ACTIVE INGREDIENTS: CAMPHOR (SYNTHETIC) 3 g/100 g; MENTHOL, UNSPECIFIED FORM 3 g/100 g; METHYL SALICYLATE 10 g/100 g
INACTIVE INGREDIENTS: CETOSTEARYL ALCOHOL; DMDM HYDANTOIN; GLUCOSAMINE SULFATE; MINERAL OIL; POLYOXYL 20 CETOSTEARYL ETHER; POLYSORBATE 20; WATER; SODIUM HYDROXIDE; STEARYL ALCOHOL; .ALPHA.-TOCOPHEROL ACETATE, D-

Valtrum® us IMMEDIATE ACTION TOPICAL ANALGESIC CREAM

Active Ingredients

Camphor 3%
Menthol 3%
Methyl salicylate 10%

Purpose

Topical analgesic

Uses

For the temporary relief of minor aches and pains of muscles and joints associated with • Simple Backache • Arthritis • Strains • Bruises • Sprains

Warnings

For external use only

• Avoid contact with eyes and mucous membranes • Do not use otherwise than as directed.
Caution: Discontinue use if excessive irritation of the skin develops.

When using this product: • Do not bandage tightly • Do not apply to wounds or damaged skin.

Stop use and ask a doctor if: • Conditions worsens • Symptoms persist for more than 7 days or clear up and occur again within a few days.

If pregnant or breast-feeding, ask a health professional before use.

Keep out of reach of children. If swallowed, get medical help, or contact a Poison Control Center right away.

Directions

Adults and Children 18 years of age and older: Apply to affected area not more than 3 to 4 times daily. Children under 18 years of age: Consult a doctor.

Other information

• Store in a cool dry place away from direct sunlight • Keep lid tightly closed

Inactive Ingredients:

Cetyl Stearyl Alcohol, DMDM Hydantoin, Glucosamine Sulfate, Mineral Oil, PEG-20 Cetyl/Stearyl Ether, Polysorbate 20, Purified Water, Sodium Hydroxide, Stearyl Alcohol, Tocopheryl Acetate.

POWERFUL ANALGESIC

NEW CREAM

santo remedio

info@quantiumlab.com

www.valtrum-santoremedio.com